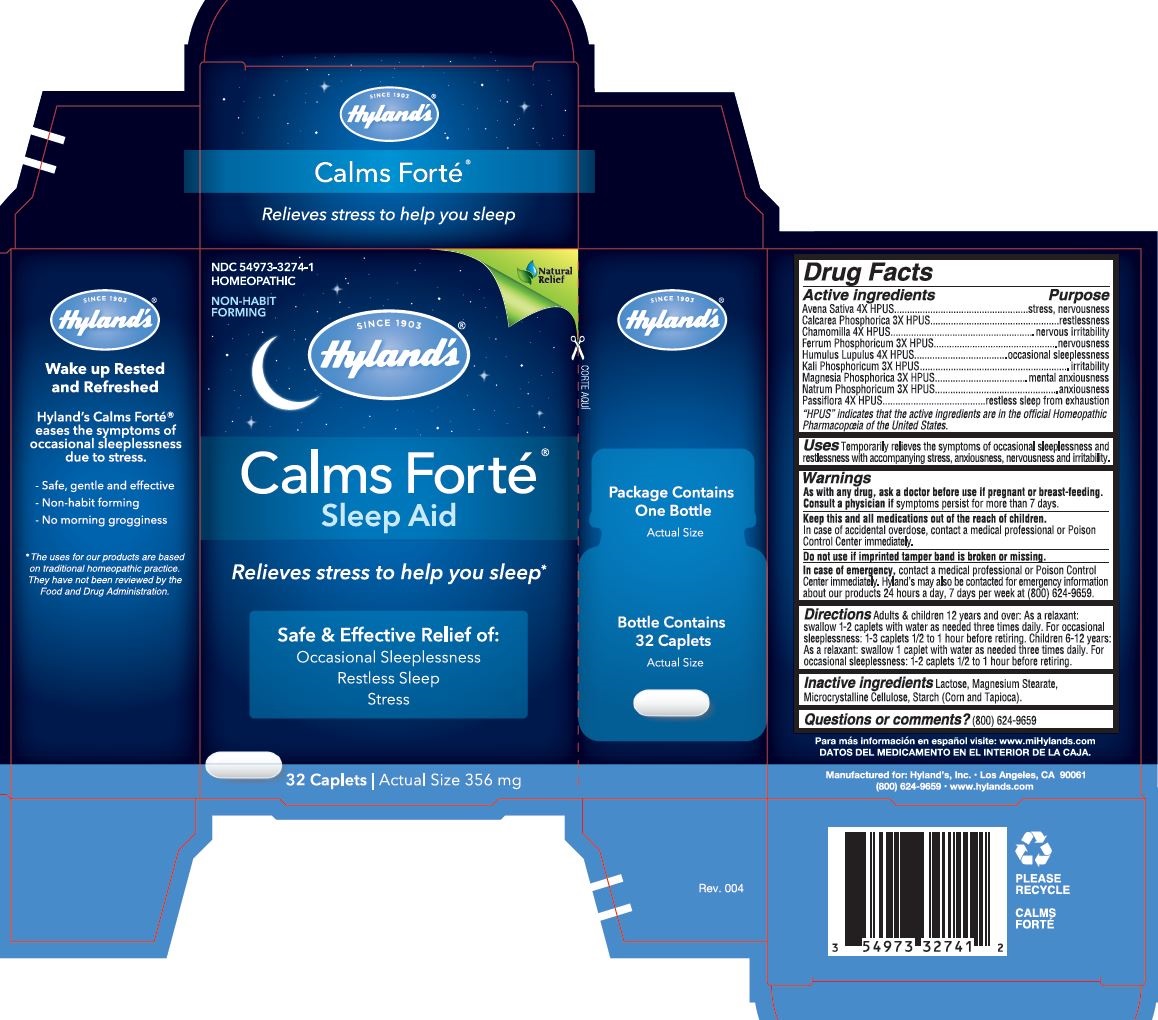 DRUG LABEL: CALMS FORTE
NDC: 54973-3274 | Form: TABLET
Manufacturer: Hyland's Inc.
Category: homeopathic | Type: HUMAN OTC DRUG LABEL
Date: 20221207

ACTIVE INGREDIENTS: AVENA SATIVA FLOWERING TOP 4 [hp_X]/1 1; TRIBASIC CALCIUM PHOSPHATE 3 [hp_X]/1 1; MATRICARIA RECUTITA 4 [hp_X]/1 1; FERROSOFERRIC PHOSPHATE 3 [hp_X]/1 1; HOPS 4 [hp_X]/1 1; POTASSIUM PHOSPHATE, DIBASIC 3 [hp_X]/1 1; MAGNESIUM PHOSPHATE, DIBASIC TRIHYDRATE 3 [hp_X]/1 1; SODIUM PHOSPHATE, DIBASIC, HEPTAHYDRATE 3 [hp_X]/1 1; PASSIFLORA INCARNATA FLOWER 4 [hp_X]/1 1
INACTIVE INGREDIENTS: LACTOSE, UNSPECIFIED FORM; MAGNESIUM PALMITOSTEARATE; CELLULOSE, MICROCRYSTALLINE; STARCH, CORN; STARCH, TAPIOCA

CALMS FORTÉ®

Drug Facts

ACTIVE INGREDIENT

Active ingredients | Purpose
Avena Sativa 4X HPUS | stress, nervousness
Calcarea Phosphorica 3X HPUS | restlessness
Chamomilla 4X HPUS | nervous irritability
Ferrum Phosphoricum 3X HPUS | nervousness
Humulus Lupulus 4X HPUS | occasional sleeplessness
Kali Phosphoricum 3X HPUS | irritability
Magnesia Phosphorica 3X HPUS | mental anxiousness
Natrum Phosphoricum 3X HPUS | anxiousness
Passiflora 4X HPUS | restless sleep from exhaustion
"HPUS" indicates the active ingredients are in the official Homeopathic Pharmacopœia of the United States.

Uses

Temporarily relieves the symptoms of occasional sleeplessness and restlessness with accompanying stress, anxiousness, nervousness and irritability.

Warnings

PREGNANCY OR BREAST FEEDING

As with any drug, ask a doctor before use if pregnant or breast-feeding.

ASK DOCTOR

Consult a physician if symptoms persist for more than 7 days.

KEEP OUT OF REACH OF CHILDREN

Keep this and all medications out of the reach of children.

In case of accidental overdose, contact a medical professional or Poison Control Center immediately.

Do not use if imprinted tamper band is broken or missing.

In case of emergency, contact a medical professional or Poison Control Center immediately. Hyland's may also be contacted for emergency information about our products 24 hours a day, 7 days per week at (800) 624-9659.

Directions

Adults & children 12 years and over: As a relaxant: swallow 1-2 caplets with water as needed three times daily. For occasional sleeplessness: 1-3 caplets 1/2 to 1 hour before retiring. Children 6-12 years: As a relaxant: swallow 1 caplet with water as needed three times daily. For occasional sleeplessness: 1-2 caplets 1/2 to 1 hour before retiring.

Inactive ingredients

Lactose, Magnesium Stearate, Microcrystalline Cellulose, Starch (Corn and Tapioca).

Questions or comments?

(800) 624-9659

PRINCIPAL DISPLAY PANEL - 32 Caplet Bottle Carton

NDC 54973-3274-1
HOMEOPATHIC

Natural
Relief

NON-HABIT
FORMING

SINCE 1903
Hyland's®

Calms Forté®
Sleep Aid

Relieves stress to help you sleep*

Safe & Effective Relief of:
Occasional Sleeplessness
Restless Sleep
Stress

32 Caplets| Actual Size 356 mg